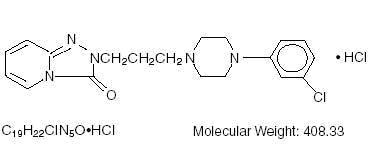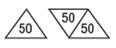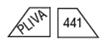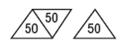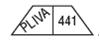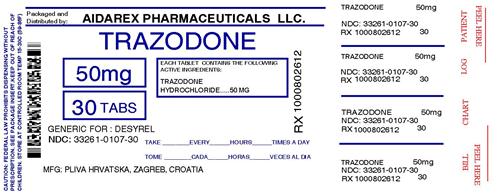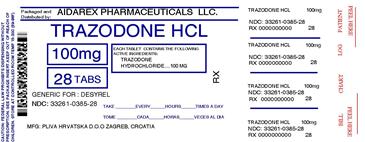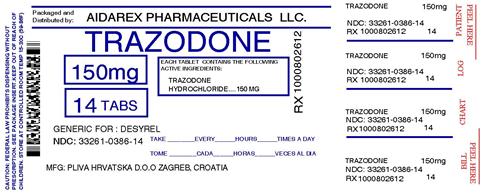 DRUG LABEL: Trazodone Hydrochloride
NDC: 33261-107 | Form: TABLET
Manufacturer: Aidarex Pharmaceuticals LLC
Category: prescription | Type: HUMAN PRESCRIPTION DRUG LABEL
Date: 20121012

ACTIVE INGREDIENTS: TRAZODONE HYDROCHLORIDE 50 mg/1 1
INACTIVE INGREDIENTS: SILICON DIOXIDE; ANHYDROUS LACTOSE; MAGNESIUM STEARATE; CELLULOSE, MICROCRYSTALLINE; SODIUM STARCH GLYCOLATE TYPE A POTATO

TRAZODONE HYDROCHLORIDE TABLETS, USP

Suicidality and Antidepressant Drugs

Antidepressants increased the risk compared to placebo of suicidal thinking and behavior (suicidality) in children, adolescents, and young adults in short-term studies of major depressive disorder (MDD) and other psychiatric disorders. Anyone considering the use of trazodone HCl or any other antidepressant in a child, adolescent, or young adult must balance this risk with the clinical need. Short-term studies did not show an increase in the risk of suicidality with antidepressants compared to placebo in adults beyond age 24; there was a reduction in risk with antidepressants compared to placebo in adults aged 65 and older. Depression and certain other psychiatric disorders are themselves associated with increases in the risk of suicide. Patients of all ages who are started on antidepressant therapy should be monitored appropriately and observed closely for clinical worsening, suicidality, or unusual changes in behavior. Families and caregivers should be advised of the need for close observation and communication with the prescriber. Trazodone HCl is not approved for use in pediatric patients. (See WARNINGS, Clinical Worsening and Suicide Risk, PRECAUTIONS, Information for Patients, and PRECAUTIONS, Pediatric Use

DESCRIPTION

Trazodone Hydrochloride Tablets USP is an antidepressant chemically unrelated to tricyclic, tetracyclic, or other known antidepressant agents. Trazodone hydrochloride is a triazolopyridine derivative designated as 2-[3-[4-(3-chlorophenyl)-1-piperazinyl]propyl]-1, 2, 4-triazolo[4, 3-a]-pyridin-3(2H)-one hydrochloride. It is a white odorless crystalline powder which is freely soluble in water. The structural formula is represented as follows:

Each tablet, for oral administration, contains 50 mg, 100 mg or 150 mg of trazodone hydrochloride, USP. In addition, each tablet contains the following inactive ingredients: colloidal silicon dioxide, lactose anhydrous, magnesium stearate, microcrystalline cellulose and sodium starch glycolate.

CLINICAL PHARMACOLOGY

The mechanism of trazodone hydrochloride’s antidepressant action in man is not fully understood. In animals, trazodone selectively inhibits its serotonin uptake by brain synaptosomes and potentiates the behavioral changes induced by the serotonin precursor, 5-hydroxytryptophan. Cardiac conduction effects of trazodone in the anesthetized dog are qualitatively dissimilar and quantitatively less pronounced than those seen with tricyclic antidepressants. Trazodone is not a monoamine oxidase inhibitor and, unlike amphetamine-type drugs, does not stimulate the central nervous system.

Pharmacokinetics

Absorption

In humans, trazodone hydrochloride is well absorbed after oral administration without selective localization in any tissue. When trazodone hydrochloride is taken shortly after ingestion of food, there may be an increase in the amount of drug absorbed, a decrease in maximum concentration and a lengthening in the time to maximum concentration. Peak plasma levels occur approximately one hour after dosing when trazodone hydrochloride is taken on an empty stomach or two hours after dosing when taken with food.

Metabolism

In vitro studies in human liver microsomes show that trazodone is metabolized to an active metabolite, m-chlorophenylpiperazine (mCPP) by cytochrome P450 3A4 (CYP3A4). Other metabolic pathways that may be involved in metabolism of trazodone have not been well characterized.

Elimination

In some patients trazodone may accumulate in the plasma.

Drug-Drug Interactions

See also PRECAUTIONS, Drug Interactions. In vitro drug metabolism studies reveal that trazodone is a substrate of the cytochrome P450 3A4 (CYP3A4) enzyme and trazodone metabolism can be inhibited by the CYP3A4 inhibitors ketoconazole, ritonavir, and indinavir. The effect of short-term administration of ritonavir (200 mg twice daily, 4 doses) on the pharmacokinetics of a single dose of trazodone (50 mg) has been studied in 10 healthy subjects. The Cmax of trazodone increased by 34%, the AUC increased 2.4-fold, the half-life increased by 2.2-fold, and the clearance decreased by 52%. Adverse effects including nausea, hypotension, and syncope were observed when ritonavir and trazodone were co-administered.

Carbamazepine induces CYP3A4. Following co-administration of carbamazepine 400 mg/day with trazodone 100 mg to 300 mg daily, carbamazepine reduced plasma concentrations of trazodone (as well as mCPP) by 76 and 60%, respectively, compared to pre-carbamazepine values.

For those patients who responded to trazodone hydrochloride, one-third of the inpatients and one-half of the outpatients had a significant therapeutic response by the end of the first week of treatment. Three-fourths of all responders demonstrated a significant therapeutic effect by the end of the second week. One-fourth of responders required 2 to 4 weeks for a significant therapeutic response.

INDICATIONS AND USAGE

Trazodone Hydrochloride Tablets USP are indicated for the treatment of depression. The efficacy of Trazodone Hydrochloride Tablets USP has been demonstrated in both inpatient and outpatient settings and for depressed patients with and without prominent anxiety. The depressive illness of patients studied corresponds to the Major Depressive Episode criteria of the American Psychiatric Association’s Diagnostic and Statistical Manual, lll.a

Major Depressive Episode implies a prominent and relatively persistent (nearly every day for at least 2 weeks) depressed or dysphoric mood that usually interferes with daily functioning, and includes at least four of the following eight symptoms: change in appetite, change in sleep, psychomotor agitation or retardation, loss of interest in usual activities or decrease in sexual drive, increased fatigability, feelings of guilt or worthlessness, slowed thinking or impaired concentration, and suicidal ideation or attempts.

CONTRAINDICATIONS

Trazodone hydrochloride tablets are contraindicated in patients hypersensitive to trazodone hydrochloride.

WARNINGS

Clinical Worsening and Suicide Risk

Patients with major depressive disorder (MDD), both adult and pediatric, may experience worsening of their depression and/or the emergence of suicidal ideation and behavior (suicidality) or unusual changes in behavior, whether or not they are taking antidepressant medications, and this risk may persist until significant remission occurs. Suicide is a known risk of depression and certain other psychiatric disorders, and these disorders themselves are the strongest predictors of suicide. There has been a long-standing concern, however, that antidepressants may have a role in inducing worsening of depression and the emergence of suicidality in certain patients during the early phases of treatment. Pooled analyses of short-term placebo-controlled trials of antidepressant drugs (SSRIs and others) showed that these drugs increase the risk of suicidal thinking and behavior (suicidality) in children, adolescents, and young adults (ages 18 to 24) with major depressive disorder (MDD) and other psychiatric disorders. Short-term studies did not show an increase in the risk of suicidality with antidepressants compared to placebo in adults beyond age 24; there was a reduction with antidepressants compared to placebo in adults aged 65 and older.

The pooled analyses of placebo-controlled trials in children and adolescents with MDD, obsessive compulsive disorder (OCD), or other psychiatric disorders included a total of 24 short-term trials of 9 antidepressant drugs in over 4400 patients. The pooled analyses of placebo-controlled trials in adults with MDD or other psychiatric disorders included a total of 295 short-term trials (median duration of 2 months) of 11 antidepressant drugs in over 77,000 patients. There was considerable variation in risk of suicidality among drugs, but a tendency toward an increase in the younger patients for almost all drugs studied. There were differences in absolute risk of suicidality across the different indications, with the highest incidence in MDD. The risk differences (drug vs placebo), however, were relatively stable within age strata and across indications. These risk differences (drug-placebo difference in the number of cases of suicidality per 1000 patients treated) are provided in Table 1.

Table 1
Age Range | Drug-Placebo Difference in; Number of Cases of Suicidality; per 1000 Patients Treated
 | Increases Compared to Placebo
<18 | 14 additional cases
18-24 | 5 additional cases
 | Decreases Compared to Placebo
25-64 | 1 fewer case
≥65 | 6 fewer cases

No suicides occurred in any of the pediatric trials. There were suicides in the adult trials, but the number was not sufficient to reach any conclusion about drug effect on suicide.

It is unknown whether the suicidality risk extends to longer-term use, i.e., beyond several months. However, there is substantial evidence from placebo-controlled maintenance trials in adults with depression that the use of antidepressants can delay the recurrence of depression.

All patients being treated with antidepressants for any indication should be monitored appropriately and observed closely for clinical worsening, suicidality, and unusual changes in behavior, especially during the initial few months of a course of drug therapy, or at times of dose changes, either increases or decreases.

The following symptoms, anxiety, agitation, panic attacks, insomnia, irritability, hostility, aggressiveness, impulsivity, akathisia (psychomotor restlessness), hypomania, and mania, have been reported in adult and pediatric patients being treated with antidepressants for major depressive disorder as well as for other indications, both psychiatric and nonpsychiatric. Although a causal link between the emergence of such symptoms and either the worsening of depression and/or the emergence of suicidal impulses has not been established, there is concern that such symptoms may represent precursors to emerging suicidality.

Consideration should be given to changing the therapeutic regimen, including possibly discontinuing the medication, in patients whose depression is persistently worse, or who are experiencing emergent suicidality or symptoms that might be precursors to worsening depression or suicidality, especially if these symptoms are severe, abrupt in onset, or were not part of the patient’s presenting symptoms.

Families and caregivers of patients being treated with antidepressants for major depressive disorder or other indications, both psychiatric and nonpsychiatric, should be alerted about the need to monitor patients for the emergence of agitation, irritability, unusual changes in behavior, and the other symptoms described above, as well as the emergence of suicidality, and to report such symptoms immediately to healthcare providers. Such monitoring should include daily observation by families and caregivers. Prescriptions for trazodone hydrochloride tablets should be written for the smallest quantity of tablets consistent with good patient management, in order to reduce the risk of overdose.

Screening Patients for Bipolar Disorder

A major depressive episode may be the initial presentation of bipolar disorder. It is generally believed (though not established in controlled trials) that treating such an episode with an antidepressant alone may increase the likelihood of precipitation of a mixed/manic episode in patients at risk for bipolar disorder. Whether any of the symptoms described above represent such a conversion is unknown. However, prior to initiating treatment with an antidepressant, patients with depressive symptoms should be adequately screened to determine if they are at risk for bipolar disorder; such screening should include a detailed psychiatric history, including a family history of suicide, bipolar disorder, and depression. It should be noted that trazodone is not approved for use in treating bipolar depression.

TRAZODONE HAS BEEN ASSOCIATED WITH THE OCCURRENCE OF PRIAPISM. IN MANY OF THE CASES REPORTED, SURGICAL INTERVENTION WAS REQUIRED AND, IN SOME OF THESE CASES, PERMANENT IMPAIRMENT OF ERECTILE FUNCTION OR IMPOTENCE RESULTED. MALE PATIENTS WITH PROLONGED OR INAPPROPRIATE ERECTIONS SHOULD IMMEDIATELY DISCONTINUE THE DRUG AND CONSULT THEIR PHYSICIAN.

The detumescence of priapism and drug-induced penile erections has been accomplished by both pharmacologic, e.g., the intracavernosal injection of alpha-adrenergic stimulants such as epinephrine and norepinephrine, as well as surgical procedures.b-g Any pharmacologic or surgical procedure utilized in the treatment of priapism should be performed under the supervision of a urologist or a physician familiar with the procedure and should not be initiated without urologic consultation if the priapism has persisted for more than 24 hours.

Trazodone hydrochloride is not recommended for use during the initial recovery phase of myocardial infarction.

Caution should be used when administering trazodone to patients with cardiac disease, and such patients should be closely monitored, since antidepressant drugs (including trazodone hydrochloride) have been associated with the occurrence of cardiac arrhythmias. Recent clinical studies in patients with pre-existing cardiac disease indicate that trazodone hydrochloride may be arrhythmogenic in some patients in that population. Arrhythmias identified include isolated PVCs, ventricular couplets, and in two patients short episodes (3 to 4 beats) of ventricular tachycardia.

PRECAUTIONS

General

Hypotension, including orthostatic hypotension and syncope, has been reported to occur in patients receiving trazodone hydrochloride. Concomitant administration of antihypertensive therapy with trazodone hydrochloride may require a reduction in the dose of the antihypertensive drug.

Little is known about the interaction between trazodone hydrochloride and general anesthetics; therefore, prior to elective surgery, trazodone hydrochloride should be discontinued for as long as clinically feasible.

As with all antidepressants, the use of trazodone hydrochloride should be based on the consideration of the physician that the expected benefits of therapy outweigh potential risk factors.

Information for Patients

Prescribers or other health professionals should inform patients, their families, and their caregivers about the benefits and risks associated with treatment with trazodone and should counsel them in its appropriate use. A patient Medication Guide about “Antidepressant Medicines, Depression and other Serious Mental Illnesses, and Suicidal Thoughts or Actions” is available for trazodone. The prescriber or health professional should instruct patients, their families, and their caregivers to read the Medication Guide and should assist them in understanding its contents. Patients should be given the opportunity to discuss the contents of the Medication Guide and to obtain answers to any questions they may have. The complete text of the Medication Guide is reprinted at the end of this document.

Patients should be advised of the following issues and asked to alert their prescriber if these occur while taking trazodone.

Clinical Worsening and Suicide Risk

Patients, their families, and their caregivers should be encouraged to be alert to the emergence of anxiety, agitation, panic attacks, insomnia, irritability, hostility, aggressiveness, impulsivity, akathisia (psychomotor restlessness), hypomania, mania, other unusual changes in behavior, worsening of depression, and suicidal ideation, especially early during antidepressant treatment and when the dose is adjusted up or down. Families and caregivers of patients should be advised to look for the emergence of such symptoms on a day-to-day basis, since changes may be abrupt. Such symptoms should be reported to the patient’s prescriber or health professional, especially if they are severe, abrupt in onset, or were not part of the patient’s presenting symptoms. Symptoms such as these may be associated with an increased risk for suicidal thinking and behavior and indicate a need for very close monitoring and possibly changes in the medication.

Other

Because priapism has been reported to occur in patients receiving trazodone hydrochloride, patients with prolonged or inappropriate penile erection should immediately discontinue the drug and consult with the physician (see WARNINGS).

Antidepressants may impair the mental and/or physical abilities required for the performance of potentially hazardous tasks, such as operating an automobile or machinery; the patient should be cautioned accordingly.

Trazodone hydrochloride may enhance the response to alcohol, barbiturates, and other CNS depressants.

Trazodone hydrochloride tablets should be given shortly after a meal or light snack. Within any individual patient, total drug absorption may be up to 20% higher when the drug is taken with food rather than on an empty stomach. The risk of dizziness/lightheadedness may increase under fasting conditions.

Laboratory Tests

Occasional low white blood cell and neutrophil counts have been noted in patients receiving trazodone hydrochloride. These were not considered clinically significant and did not necessitate discontinuation of the drug; however, the drug should be discontinued in any patient whose white blood cell count or absolute neutrophil count falls below normal levels. White blood cell and differential counts are recommended for patients who develop fever and sore throat (or other signs of infection) during therapy.

Drug Interactions

In vitro drug metabolism studies suggest that there is a potential for drug interactions when trazodone is given with CYP3A4 inhibitors. Ritonavir, a potent CYP3A4 inhibitor, increased the Cmax, AUC, and elimination half-life, and decreased clearance of trazodone after administration of ritonavir twice daily for 2 days. Adverse effects including nausea, hypotension, and syncope were observed when ritonavir and trazodone were co-administered. It is likely that ketoconazole, indinavir, and other CYP3A4 inhibitors such as itraconazole or nefazodone may lead to substantial increases in trazodone plasma concentrations, with the potential for adverse effects. If trazodone is used with a potent CYP3A4 inhibitor, a lower dose of trazodone should be considered.

Carbamazepine reduced plasma concentrations of trazodone when co-administered. Patients should be closely monitored to see if there is a need for an increased dose of trazodone when taking both drugs.

Increased serum digoxin or phenytoin levels have been reported to occur in patients receiving trazodone hydrochloride concurrently with either of those two drugs. It is not known whether interactions will occur between monoamine oxidase (MAO) inhibitors and trazodone hydrochloride. Due to the absence of clinical experience, if MAO inhibitors are discontinued shortly before or are to be given concomitantly with trazodone hydrochloride, therapy should be initiated cautiously with gradual increase in dosage until optimum response is achieved.

Therapeutic Interactions

Concurrent administration with electroshock therapy should be avoided because of the absence of experience in this area.

There have been reports of increased and decreased prothrombin time occurring in warfarinized patients who take trazodone.

Carcinogenesis, Mutagenesis, Impairment of Fertility

No drug- or dose-related occurrence of carcinogenesis was evident in rats receiving trazodone hydrochloride in daily oral doses up to 300 mg/kg for 18 months.

Pregnancy

Teratogenic Effects

Pregnancy Category C

Trazodone hydrochloride has been shown to cause increased fetal resorption and other adverse effects on the fetus in two studies using the rat when given at dose levels approximately 30 to 50 times the proposed maximum human dose. There was also an increase in congenital anomalies in one of three rabbit studies at approximately 15 to 50 times the maximum human dose. There are no adequate and well-controlled studies in pregnant women. Trazodone hydrochloride should be used during pregnancy only if the potential benefit justifies the potential risk to the fetus.

Nursing Mothers

Trazodone hydrochloride and/or its metabolites have been found in the milk of lactating rats, suggesting that the drug may be secreted in human milk. Caution should be exercised when trazodone hydrochloride is administered to a nursing woman.

Pediatric Use

Safety and effectiveness in the pediatric population have not been established (see BOX WARNINGS and WARNINGS, Clinical Worsening and Suicide Risk).

Anyone considering the use of trazodone hydrochloride tablets in a child or adolescent must balance the potential risks with the clinical need.

ADVERSE REACTIONS

Because the frequency of adverse drug effects is affected by diverse factors (e.g., drug dose, method of detection, physician judgment, disease under treatment, etc.) a single meaningful estimate of adverse event incidence is difficult to obtain. This problem is illustrated by the variation in adverse event incidence observed and reported from the inpatients and outpatients treated with trazodone hydrochloride. It is impossible to determine precisely what accounts for the differences observed.

Clinical Trial Reports

The table below is presented solely to indicate the relative frequency of adverse events reported in representative controlled clinical studies conducted to evaluate the safety and efficacy of trazodone hydrochloride.

The figures cited cannot be used to predict concisely the incidence of untoward events in the course of usual medical practice where patient characteristics and other factors often differ from those which prevailed in the clinical trials. These incidence figures, also, cannot be compared with those obtained from other clinical studies involving related drug products and placebo as each group of drug trials is conducted under a different set of conditions.

Table 2
Treatment Emergent
Symptom Incidence
 | Inpatients |  | Outpatients
 | T [T=Trazodone HCl] | P [P=Placebo] | T | P
Number of Patients | 142 | 95 | 157 | 158
% of Patients Reporting Allergic
Skin Condition/Edema | 2.8 | 1.1 | 7.0 | 1.3
Autonomic
Blurred Vision | 6.3 | 4.2 | 14.7 | 3.8
Constipation | 7.0 | 4.2 | 7.6 | 5.7
Dry Mouth | 14.8 | 8.4 | 33.8 | 20.3
Cardiovascular
Hypertension | 2.1 | 1.1 | 1.3 | * [Incidence less than 1 %]
Hypotension | 7.0 | 1.1 | 3.8 | 0.0
Shortness of Breath | * | 1.1 | 1.3 | 0.0
Syncope | 2.8 | 2.1 | 4.5 | 1.3
Tachycardia/Palpitations | 0.0 | 0.0 | 7.0 | 7.0
CNS
Anger/Hostility | 3.5 | 6.3 | 1.3 | 2.5
Confusion | 4.9 | 0.0 | 5.7 | 7.6
Decreased Concentration | 2.8 | 2.1 | 1.3 | 0.0
Disorientation | 2.1 | 0.0 | * | 0.0
Dizziness/Lightheadedness | 19.7 | 5.3 | 28.0 | 15.2
Drowsiness | 23.9 | 6.3 | 40.8 | 19.6
Excitement | 1.4 | 1.1 | 5.1 | 5.7
Fatigue | 11.3 | 4.2 | 5.7 | 2.5
Headache | 9.9 | 5.3 | 19.8 | 15.8
Insomnia | 9.9 | 10.5 | 6.4 | 12.0
Impaired Memory | 1.4 | 0.0 | * | *
Nervousness | 14.8 | 10.5 | 6.4 | 8.2
Gastrointestinal
Abdominal/Gastric Disorder | 3.5 | 4.2 | 5.7 | 4.4
Bad Taste in Mouth | 1.4 | 0.0 | 0.0 | 0.0
Diarrhea | 0.0 | 1.1 | 4.5 | 1.9
Nausea/Vomiting | 9.9 | 1.1 | 12.7 | 9.5
Musculoskeletal
Musculoskeletal Aches/Pains | 5.6 | 3.2 | 5.1 | 2.5
Neurological
Incoordination | 4.9 | 0.0 | 1.9 | 0.0
Paresthesia | 1.4 | 0.0 | 0.0 | *
Tremors | 2.8 | 1.1 | 5.1 | 3.8
Sexual Function
Decreased Libido | * | 1.1 | 1.3 | *
Other
Decreased Appetite | 3.5 | 5.3 | 0.0 | *
Eyes Red/Tired/Itching | 2.8 | 0.0 | 0.0 | 0.0
Head Full-Heavy | 2.8 | 0.0 | 0.0 | 0.0
Malaise | 2.8 | 0.0 | 0.0 | 0.0
Nasal/Sinus Congestion | 2.8 | 0.0 | 5.7 | 3.2
Nightmares/Vivid Dreams | * | 1.1 | 5.1 | 5.7
Sweating/Clamminess | 1.4 | 1.1 | * | *
Tinnitus | 1.4 | 0.0 | 0.0 | *
Weight Gain | 1.4 | 0.0 | 4.5 | 1.9
Weight Loss | * | 3.2 | 5.7 | 2.5

Occasional sinus bradycardia has occurred in long-term studies.

In addition to the relatively common (i.e., greater than 1%) untoward events enumerated above, the following adverse events have been reported to occur in association with the use of trazodone hydrochloride in the controlled clinical studies: akathisia, allergic reaction, anemia, chest pain, delayed urine flow, early menses, flatulence, hallucinations/delusions, hematuria, hyper-salivation, hypomania, impaired speech, impotence, increased appetite, increased libido, increased urinary frequency, missed periods, muscle twitches, numbness, and retrograde ejaculation.

Post Introduction Reports

Although the following adverse reactions have been reported in trazodone hydrochloride users, the causal association has neither been confirmed nor refuted.

Voluntary reports received since market introduction include the following: abnormal dreams, agitation, alopecia, anxiety, aphasia, apnea, ataxia, breast enlargement or engorgement, cardiospasm, cerebrovascular accident, chills, cholestatis, clitorism, congestive heart failure, diplopia, edema, extrapyramidal symptoms, grand mal seizures, hallucinations, hemolytic anemia, hirsutism, hyperbilirubinemia, increased amylase, increased salivation, insomnia, leukocytosis, leukonychia, jaundice, lactation, liver enzyme alterations, methemoglobinemia, nausea/vomiting (most frequently), paresthesia, paranoid reaction, priapism (see WARNINGS and PRECAUTIONS, Information for Patients; some patients have required surgical intervention), pruritus, psoriasis, psychosis, rash, stupor, inappropriate ADH syndrome, tardive dyskinesia, unexplained death, urinary incontinence, urinary retention, urticaria, vasodilation, vertigo, and weakness.

Cardiovascular system effects which have been reported include the following: conduction block, orthostatic hypotension and syncope, palpitations, bradycardia, atrial fibrillation, myocardial infarction, cardiac arrest, arrhythmia, and ventricular ectopic activity, including ventricular tachycardia (see WARNINGS).

OVERDOSAGE

Animal Oral LD50

The oral LD50 of the drug is 610 mg/kg in mice, 486 mg/kg in rats, and 560 mg/kg in rabbits.

Signs and Symptoms

Death from overdose has occurred in patients ingesting trazodone hydrochloride and other drugs concurrently (namely, alcohol; alcohol + chloral hydrate + diazepam; amobarbital; chlordiazepoxide; or meprobamate).

The most severe reactions reported to have occurred with overdose of trazodone hydrochloride alone have been priapism, respiratory arrest, seizures, and EKG changes. The reactions reported most frequently have been drowsiness and vomiting. Overdosage may cause an increase in incidence or severity of any of the reported adverse reactions (see ADVERSE REACTIONS).

Treatment

There is no specific antidote for trazodone hydrochloride. Treatment should be symptomatic and supportive in the case of hypotension or excessive sedation. Any patient suspected of having taken an overdose should have the stomach emptied by gastric lavage. Forced diuresis may be useful in facilitating elimination of the drug.

DOSAGE AND ADMINISTRATION

The dosage should be initiated at a low level and increased gradually, noting the clinical response and any evidence of intolerance. Occurrence of drowsiness may require the administration of a major portion of the daily dose at bedtime or a reduction of dosage. Trazodone Hydrochloride Tablets USP should be taken shortly after a meal or light snack. Symptomatic relief may be seen during the first week, with optimal antidepressant effects typically evident within two weeks. Twenty-five percent of those who respond to Trazodone Hydrochloride Tablets USP require more than two weeks (up to four weeks) of drug administration.

Usual Adult Dosage

An initial dose of 150 mg/day in divided doses is suggested. The dose may be increased by 50 mg/day every three to four days. The maximum dose for outpatients usually should not exceed 400 mg/day in divided doses. Inpatients (i.e., more severely depressed patients) may be given up to but not in excess of 600 mg/day in divided doses.

Maintenance

Dosage during prolonged maintenance therapy should be kept at the lowest effective level. Once an adequate response has been achieved, dosage may be gradually reduced, with subsequent adjustment depending on therapeutic response.

Although there has been no systematic evaluation of the efficacy of Trazodone Hydrochloride Tablets USP beyond 6 weeks, it is generally recommended that a course of antidepressant drug treatment should be continued for several months.

HOW SUPPLIED

Trazodone Hydrochloride Tablets USP:

50 mg - White, round, scored, compressed tablets. Imprinted PLIVA 433

Available in bottles of 10, 20, 28, 30, 60, 90, and 120 Tablets

100 mg - White, round, scored, compressed tablets. Imprinted PLIVA 434

Available in bottles of 14, 30 and 60 Tablets.

150 mg - White, trapezoid, bisected on one side, trisected on the other side. Imprinted PLIVA 441 on one side and 50 in each triangular segment on the other side.

Available in bottles of 14, 30 and 60 Tablets.

Directions for using the correct score when breaking the tablet please refer to the following:

-For 50 mg, break the score on either the left or right side of the tablet (one-third of a tablet).

-For 75 mg, break the score down the middle of the tablet (one-half of a tablet).

-For 100 mg, break the score on either the left or right side of the tablet (two-thirds of a tablet).

-For 150 mg, use the entire tablet.

Dispense in a tight, light-resistant container as defined in the USP, with a child-resistant closure (as required).

Store at 20° to 25°C (68° to 77°F) [See USP Controlled Room Temperature].

REFERENCES

(a) Williams JBW, Ed: Diagnostic and Statistical Manual of Mental Disorders-III, American Psychiatric Association, May 1980. (b) Lue TF, Physiology of erection and pathophysiology of impotence. In: Wash PC, Retik AB, Stamey TA, Vaughan ED, eds. Campbell’s Urology. Sixth edition. Philadelphia: W.B. Saunders: 1992: 722-725. (c) Goldstein I, Krane RJ, Diagnosis and therapy of erectile dysfunction. In: Wash PC, Retik AB, Stamey TA, Vaughan ED, eds. Campbell’s Urology. Sixth edition. Philadelphia: W.B. Saunders: 1992: 3071-3072. (d) Yealy DM, Hogya PT: Priapism. Emerg Med Clin North Am, 1988: 6:509-520. (e) Banos JE, Bosch F, Farre M. Drug-induced priapism. Its aetiology, incidence and treatment. Med Toxicol Adverse Drug Exp. 1989: 4:46-58. (f) O’Brien WM, O’Connor KP, Lynch JH. Priapism: current concepts. Ann Emerg Med. 1989: 980-983. (g) Bardin ED, Krieger JN. Pharmacological priapism: comparison of trazodone- and papaverine-associated cases. Int Urol Nephrol. 1990: 22:147-152.

Manufactured In Croatia By:

PLIVA HRVATSKA d.o.o.

Zagreb, Croatia

Manufactured For:

TEVA PHARMACEUTICALS USA

Sellersville, PA 18960

Repackaged By:
Aidarex Pharmaceuticals, LLC.
Corona, CA 92880

Iss. 2/2010

FLEXIDOSE® is a registered trademark of PLIVA®, Inc. for its tablets. The trapezoidal shaped tablet is a trademark and original design of PLIVA® Inc.

Medication Guide

Antidepressant Medicines, Depression and other Serious Mental Illnesses, and Suicidal Thoughts or Actions

Read the Medication Guide that comes with your or your family member’s antidepressant medicine. This Medication Guide is only about the risk of suicidal thoughts and actions with antidepressant medicines. Talk to your, or your family member’s, healthcare provider about:

• all risks and benefits of treatment with antidepressant medicines

• all treatment choices for depression or other serious mental illness

What is the most important information I should know about antidepressant medicines, depression and other serious mental illnesses, and suicidal thoughts or actions?

1. Antidepressant medicines may increase suicidal thoughts or actions in some children, teenagers, and young adults within the first few months of treatment.

2. Depression and other serious mental illnesses are the most important causes of suicidal thoughts and actions. Some people may have a particularly high risk of having suicidal thoughts or actions. These include people who have (or have a family history of) bipolar illness (also called manic-depressive illness) or suicidal thoughts or actions.

3. How can I watch for and try to prevent suicidal thoughts and actions in myself or a family member?

• Pay close attention to any changes, especially sudden changes, in mood, behaviors, thoughts, or feelings. This is very important when an antidepressant medicine is started or when the dose is changed.

• Call the healthcare provider right away to report new or sudden changes in mood, behavior, thoughts, or feelings.

• Keep all follow-up visits with the healthcare provider as scheduled. Call the healthcare provider between visits as needed, especially if you have concerns about symptoms.

Call a healthcare provider right away if you or your family member has any of the following symptoms, especially if they are new, worse, or worry you:

- thoughts about suicide or dying
- attempts to commit suicide
- new or worse depression
- new or worse anxiety
- feeling very agitated or restless
- panic attacks
- trouble sleeping (insomnia)
- new or worse irritability
- acting aggressive, being angry, or violent
- acting on dangerous impulses
- an extreme increase in activity and talking (mania)
- other unusual changes in behavior or mood

What else do I need to know about antidepressant medicines?

• Never stop an antidepressant medicine without first talking to a healthcare provider. Stopping an antidepressant medicine suddenly can cause other symptoms.

• Antidepressants are medicines used to treat depression and other illnesses. It is important to discuss all the risks of treating depression and also the risks of not treating it. Patients and their families or other caregivers should discuss all treatment choices with the healthcare provider, not just the use of antidepressants.

• Antidepressant medicines have other side effects. Talk to the healthcare provider about the side effects of the medicine prescribed for you or your family member.

• Antidepressant medicines can interact with other medicines. Know all of the medicines that you or your family member takes. Keep a list of all medicines to show the healthcare provider. Do not start new medicines without first checking with your healthcare provider.

• Not all antidepressant medicines prescribed for children are FDA approved for use in children. Talk to your child’s healthcare provider for more information.

Call your doctor for medical advice about side effects. You may report side effects to FDA at 1-800-FDA-1088.

This Medication Guide has been approved by the U.S. Food and Drug Administration for all antidepressants.

Manufactured In Croatia By:

PLIVA HRVATSKA d.o.o.

Zagreb, Croatia

Manufactured For:

TEVA PHARMACEUTICALS USA

Sellersville, PA 18960

Rev. E 5/2008

11001630

PRINCIPAL DISPLAY PANEL

Trazodone Hydrochloride Tablets USP 50 mg 100 Tablets Label Text

NDC 50111-443-01

TraZODONE

HYDROCHLORIDE

Tablets USP

50 mg

PHARMACIST: Dispense the

Medication Guide provided

separately to each patient.

Rx only

100 Tablets

TEVA

PRINCIPAL DISPLAY PANEL

Trazodone Hydrochloride Tablets USP 100 mg 100 Tablets Label Text

NDC 50111-434-01

TraZODONE

HYDROCHLORIDE

Tablets USP

100 mg

PHARMACIST: Dispense the Medication

Guide provided separately to each patient.

Rx only

100 Tablets

TEVA

PRINCIPAL DISPLAY PANEL

Trazodone Hydrochloride Tablets USP 150 mg 100 Tablets Label Text

NDC 50111-441-01

TraZODONE

HYDROCHLORIDE

Tablets USP

150 mg

PHARMACIST: Dispense the

Medication Guide provided

separately to each patient.

Rx only

100 Tablets

TEVA